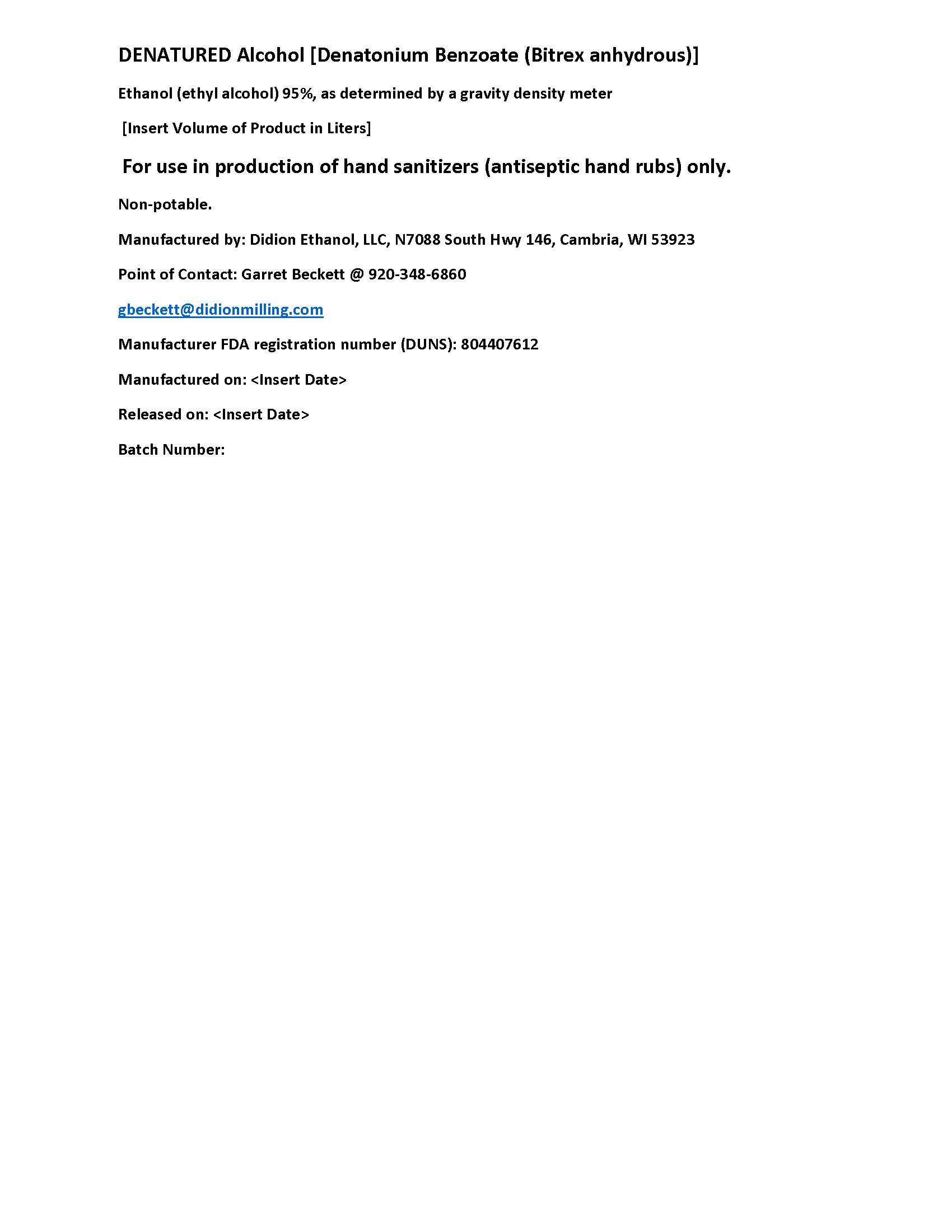 DRUG LABEL: BTS-72
NDC: 74519-000 | Form: LIQUID
Manufacturer: Didion Ethanol, LLC
Category: otc | Type: HUMAN OTC DRUG LABEL
Date: 20200401

ACTIVE INGREDIENTS: ALCOHOL 95 L/100 L
INACTIVE INGREDIENTS: WATER; DENATONIUM BENZOATE ANHYDROUS 0.000488336 L/100 L

Alcohol for Hand Sanitizer

This is a denatured ethanol manufactured for a hand sanitizer according to the Temporary Policy for Preparation of Certain Alcohol-Based Hand Sanitizer Products During the Public Health Emergency (CoViD-19); Guidance for Industry.

The denatured ethanol is manufactured using only the following United States Pharmacopoeia (USP) grade ingredients in the preparation of the product (percentage in final product formulation) consistent with World Health Organization (WHO) recommendations:

1. Alcohol (ethanol) (USP or Food Chemical Codex (FCC) grade) (95%, volume/volume (v/v)) in an aqueous solution denatured according to Alcohol and Tobacco Tax and Trade Bureau regulations in 27 CFR part 20.

The firm does not add other active or inactive ingredients. Different or additional ingredients may impact the quality and potency of the product.

Active Ingredient(s)

Alcohol 95% v/v. Purpose: Antiseptic

Purpose

For use in production of Antiseptic, Hand Sanitizer

Use

Denatured Ethanol for use in production of Hand Sanitizer to help reduce bacteria that potentially can cause disease. For use when soap and water are not available.

Warnings

For external use only. Flammable. Keep away from heat or flame

Do not use

- in children less than 2 months of age
- on open skin wounds

When using this product keep out of eyes, ears, and mouth. In case of contact with eyes, rinse eyes thoroughly with water.
Stop use and ask a doctor if irritation or rash occurs. These may be signs of a serious condition.
Keep out of reach of children. If swallowed, get medical help or contact a Poison Control Center right away.

Stop use and ask a doctor if irritation or rash occurs. These may be signs of a serious condition.

Keep out of reach of children. If swallowed, get medical help or contact a Poison Control Center right away.

Directions

- For use in production of Hand Sanitizer that meets the Temporary Policy for Preparation of Certain Alcohol-Based Hand Sanitizer Products During the Public Health Emergency (CoViD-19); Guidance for Industry.

Other information

- Store between 15-30C (59-86F)
- Avoid freezing and excessive heat above 40C (104F)

Inactive ingredients

Denatonium Benzoate